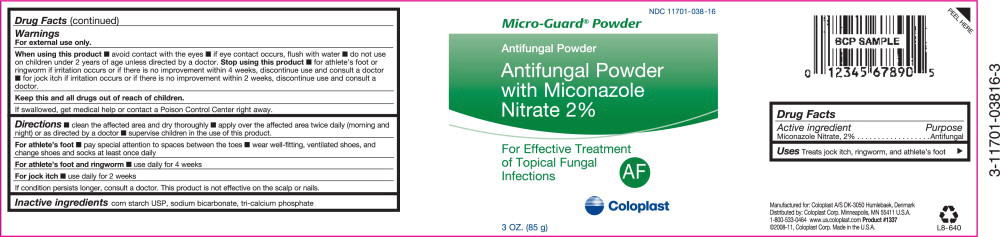 DRUG LABEL: Micro-Guard 
NDC: 11701-038 | Form: POWDER
Manufacturer: Coloplast Manufacturing US, LLC
Category: otc | Type: HUMAN OTC DRUG LABEL
Date: 20231214

ACTIVE INGREDIENTS: MICONAZOLE NITRATE 20 mg/1 g
INACTIVE INGREDIENTS: STARCH, CORN; SODIUM BICARBONATE; TRIBASIC CALCIUM PHOSPHATE

Micro-Guard® Powder
Antifungal Powder
With Miconazole
Nitrate 2%

For Effective Treatment of Topical Fungal Infections
AF

Drug Facts

Active ingredient

Miconazole Nitrate, 2%

Purpose

Antifungal

INDICATIONS AND USAGE

Uses Treats jock itch, ringworm, and athlete's foot ►

Warnings

For external use only.

When using this product

- avoid contact with the eyes
- if eye contact occurs, flush with water
- do not use on children under 2 years of age unless directed by a doctor.

Stop using this product

- for athlete's foot or ringworm if irritation occurs or if there is no improvement within 4 weeks, discontinue use and consult a doctor
- for jock itch if irritation occurs or if there is no improvement within 2 weeks, discontinue use and consult a doctor.

KEEP OUT OF REACH OF CHILDREN

Keep this and all drugs out of reach of children.

If swallowed, get medical help or contact a Poison Control Center right away.

Directions

- clean the affected area and dry thoroughly
- apply over the affected area twice daily (morning and night) or as directed by a doctor
- supervise children in the use of this product.

For athlete's foot

- pay special attention to spaces between the toes
- wear well-fitting, ventilated shoes, and change shoes and socks at least once daily

For athlete's foot and ringworm

- use daily for 4 weeks

For jock itch

- use daily for 2 weeks

If condition persists longer, consult a doctor. This product is not effective on the scalp or nails.

INACTIVE INGREDIENT

Inactive ingredients corn starch USP, sodium bicarbonate, tri-calcium phosphate

Manufactured for Coloplast A/S DK-3050 Humlebaek, Denmark
Distributed by: Coloplast Corp. Minneapolis, MN 55411 U.S.A.
1-800-533-0464 www.us.coloplast.com Product #1337

©2008-11, Coloplast Corp. Made in the U.SA

PACKAGE LABEL

PRINCIPAL DISPLAY PANEL - 3 OZ. (85 g)

NDC 11701-038-16

Micro-Guard® Powder
Antifungal Powder
With Miconazole
Nitrate 2%

For Effective Treatment of Topical Fungal Infections

AF

Coloplast

3 OZ. (85 g)

L8-640